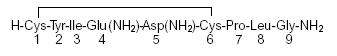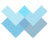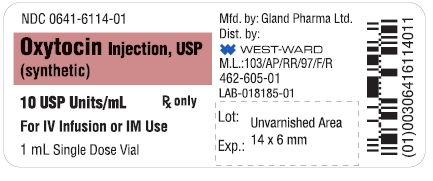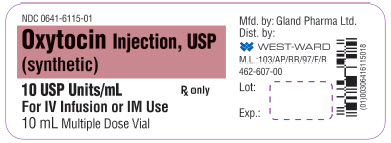 DRUG LABEL: Oxytocin
NDC: 0641-6114 | Form: INJECTION
Manufacturer: Hikma Pharmaceuticals USA Inc.
Category: prescription | Type: HUMAN PRESCRIPTION DRUG LABEL
Date: 20191230

ACTIVE INGREDIENTS: OXYTOCIN 10 [USP'U]/1 mL
INACTIVE INGREDIENTS: CHLOROBUTANOL 500 mg/1 mL; ACETIC ACID; WATER

Oxytocin Injection, USP (synthetic)

FOR INTRAVENOUS INFUSION OR INTRAMUSCULAR USE

Rx only

DESCRIPTION

Each mL of Oxytocin Injection sterile solution contains an oxytocic activity equivalent to 10 USP Posterior Pituitary Units, Chlorobutanol (a chloroform derivative), 0.5%, as a preservative, and acetic acid to adjust pH (3.0 to 5.0). Oxytocin is intended for IM or IV use. Oxytocin is a synthetic polypeptide; it occurs as a white powder and is soluble in water. It may be designated chemically as:

CLINICAL PHARMACOLOGY

The pharmacologic and clinical properties of oxytocin are identical with those of naturally occurring oxytocin principle of the posterior lobe of pituitary. Oxytocin exerts a selective action on the smooth musculature of the uterus, particularly toward the end of pregnancy, during labor, and immediately following delivery. Oxytocin stimulates rhythmic contractions of the uterus, increases the frequency of existing contractions, and raises the tone of the uterine musculature.

When given in appropriate doses during pregnancy, oxytocin is capable of eliciting graded increases in uterine motility from a moderate increase in the rate and force of spontaneous motor activity to sustained titanic contraction. The sensitivity of the uterus to oxytocic activity increases progressively throughout pregnancy until term when it is maximal.

Oxytocin is distributed throughout the extracellular fluid. Small amounts of this drug probably reach the fetal circulation. Oxytocin has a plasma half-life of about 3 to 5 minutes. Following parenteral administration, uterine response occurs within 3 to 5 minutes and persists for 2 to 3 hours. Its rapid removal from plasma is accomplished largely by the kidney and the liver. Only small amounts oxytocin are excreted in the urine unchanged.

INDICATIONS AND USAGE

BOXED WARNING

IMPORTANT NOTICE
Oxytocin is indicated for the medical rather than the elective induction of labor. Available data and information are inadequate to define the benefits-to-risks considerations in the use of the drug product for elective induction. Elective induction of labor is defined as the initiation of labor for convenience in an individual with a term pregnancy who is free of medical indications.

Antepartum

Oxytocin is indicated for the initiation or improvement of uterine contractions, where this is desirable and considered suitable for reasons of fetal or maternal concern, in order to achieve early vaginal delivery. It is indicated for (1) induction of labor in patients with a medical indication for the initiation of labor, such as Rh problems, maternal diabetes, preeclampsia at or near term, when delivery is in the best interests of mother and fetus or when membranes are prematurely ruptured and delivery is indicated; (2) stimulation or reinforcement of labor, as in selected cases of uterine inertia; (3) as adjunctive therapy in the management of incomplete or inevitable abortion. In the first trimester, curettage is generally considered primary therapy. In second trimester abortion, oxytocin infusion will often be successful in emptying the uterus. Other means of therapy, however, may be required in such cases.

Postpartum

Oxytocin is indicated to produce uterine contractions during the third stage of labor and to control postpartum bleeding or hemorrhage.

CONTRAINDICATIONS

Oxytocin is contraindicated in any of the following conditions:

significant cephalopelvic disproportion;

unfavorable fetal positions or presentations which are undeliverable without conversion prior to delivery, e.g., transverse lies;

in obstetrical emergencies where the benefit-to-risk ratio for either the fetus or the mother favors surgical intervention;

in cases of fetal distress where delivery is not imminent;

hypertonic uterine patterns;

hypersensitivity to the drug.

Prolonged use in uterine inertia or severe toxemia is contraindicated.

Oxytocin should not be used in cases where vaginal delivery is not indicated, such as cord presentation or prolapse, total placenta previa, and vasa previa.

WARNINGS

Oxytocin, when given for induction or stimulation of labor, must be administered only by intravenous infusion (drip method) and with adequate medical supervision in a hospital.

PRECAUTIONS

General

1. All patients receiving intravenous infusions of oxytocin must be under continuous observation by trained personnel with a thorough knowledge of the drug and are qualified to identify complications. A physician qualified to manage any complications should be immediately available.
2. When properly administered, oxytocin should stimulate uterine contractions similar to those seen in normal labor. Overstimulation of the uterus by improper administration can be hazardous to both mother and fetus. Even with proper administration and adequate supervision, hypertonic contractions can occur in patients whose uteri are hypersensitive to oxytocin.
3. Except in unusual circumstances, oxytocin should not be administered in the following conditions: prematurity, borderline cephalopelvic disproportion, previous major surgery on the cervix or uterus, including cesarean section, overdistention of the uterus, grand multiparity, or invasive cervical carcinoma. Because of the variability of the combinations of factors which may be present in the conditions listed above, the definition of “unusual circumstances” must be left to the judgment of the physician. The decision can only be made by carefully weighing the potential benefits which oxytocin can provide in a given case against the rare occurrence of hypertonicity or tetanic spasm with this drug.
4. Maternal deaths due to hypertensive episodes, subarachnoid hemorrhage, rupture of the uterus, and fetal deaths and permanent CNS or brain damage of the infant due to various causes have been reported to be associated with the use of parenteral oxytocic drugs for induction of labor or for augmentation in the first and second stages of labor.
5. Oxytocin has been shown to have an intrinsic antidiuretic effect, acting to increase water reabsorption from the glomerular filtrate. Consideration should, therefore, be given to the possibility of water intoxication, particularly when oxytocin is administered continuously by infusion and the patient is receiving fluids by mouth.
6. Oxytocin should be considered for use only in patients who have been carefully selected. Pelvic adequacy must be considered and maternal and fetal conditions thoroughly evaluated before use of the drug.

Drug Interactions

Severe hypertension has been reported when oxytocin was given three to four hours following prophylactic administration of a vasoconstrictor in conjunction with caudal-block anesthesia. Cyclopropane anesthesia may modify oxytocin’s cardiovascular effects, so as to produce unexpected results such as hypotension. Maternal sinus bradycardia with abnormal atrioventricular rhythms has also been noted when oxytocin was used concomitantly with cyclopropane anesthesia.

Carcinogenesis, Mutagenesis, Impairment of Fertility

There are no animal or human studies on the carcinogenicity and mutagenicity of this drug, nor is there any information on its effect on fertility.

Pregnancy

PREGNANCY CATEGORY C.

There are no known indications for use of oxytocin in the first and second trimester of pregnancy other than in relation to spontaneous or induced abortion. Based on the wide experience with this drug and its chemical structure and pharmacological properties, it would not be expected to present a risk of fetal abnormalities when used as indicated.

NONTERATOGENIC EFFECTS

See “ADVERSE REACTIONS” in the fetus or infant.

Labor and Delivery

See “INDICATIONS AND USAGE”

Nursing Mothers

It is not known whether this drug is excreted in human milk. Because many drugs are excreted in human milk, caution should be exercised when oxytocin is administered to a nursing woman.

ADVERSE REACTIONS

The following adverse reactions have been reported in the mother:

Anaphylactic reaction Nausea

Postpartum hemorrhage Vomiting

Cardiac arrhythmia Premature ventricular contractions

Fatal afibrinogenemia Pelvic hematoma

Excessive dosage or hypersensitivity to the drug may result in uterine hypertonicity, spasm, tetanic contraction, or rupture of the uterus.

The possibility of increased blood loss and afibrinogenemia should be kept in mind when administering the drug.

Severe water intoxication with convulsions and coma has occurred, associated with a slow oxytocin infusion over a 24-hour period. Maternal death due to oxytocin-induced water intoxication has been reported.

The following adverse reactions have been reported in the fetus or infant:

(Due to induced uterine motility)

Bradycardia

Premature ventricular contractions and other arrhythmias

Permanent CNS or brain damage

Fetal death

(Due to use of oxytocin in the mother)

Low Apgar scores at five minutes

Neonatal jaundice

Neonatal retinal hemorrhage

OVERDOSAGE

Overdosage with oxytocin depends essentially on uterine hyperactivity whether or not due to hypersensitivity to this agent. Hyperstimulation with strong (hypertonic) or prolonged (tetanic) contractions, or a resting tone of 15 to 20 mm H2O or more between contractions can lead to tumultuous labor, uterine rupture, cervical and vaginal lacerations, postpartum hemorrhage, utero-placental hypoperfusion, and variable deceleration of fetal heart, fetal hypoxia, hypercapnia, or death. Water intoxication with convulsions, which is caused by the inherent antidiuretic effect of oxytocin, is a serious complication that may occur if large doses (40 to 50 milliunits/minute) are infused for long periods. Management consists of immediate discontinuation of oxytocin and symptomatic and supportive therapy.

DOSAGE AND ADMINISTRATION

Parenteral drug products should be inspected visually for particulate matter and discoloration prior to administration, whenever solution and container permit.

Dosage of oxytocin is determined by the uterine response. The following dosage information is based upon various regimens and indications in general use.

A. Induction or Stimulation of Labor

Intravenous infusion (drip method) is the only acceptable method of administration for the induction or stimulation of labor.

Accurate control of the rate of infusion flow is essential. An infusion pump or other such device and frequent monitoring of strength of contractions and fetal heart rate are necessary for the safe administration of oxytocin for the induction or stimulation of labor. If uterine contractions become too powerful, the infusion can be abruptly stopped, and oxytocic stimulation of the uterine musculature will soon wane.

1. An intravenous infusion of nonoxytocin-containing solution should be started. Physiologic electrolyte solution should be used except under unusual circumstances.
2. To prepare the usual solution for infusion, 1-mL Oxytocin Injection, 10 USP Units/mL is combined aseptically with 1,000 mL of nonhydrating diluent (physiologic electrolyte solution). The combined solution, rotated in the infusion bottle to ensure thorough mixing, containing 10 mU/mL. Add the container with dilute oxytocic solution to the system through use of a constant infusion pump or other such device, to control accurately the rate of infusion.
3. The initial dose should be no more than 1 to 2 mU/min. the dose may be gradually increased in increments of no more than 1 to 2 mU/min. until a contraction pattern has been established which is similar to normal labor.
4. The fetal heart rate, resting uterine tone, and the frequency, duration, and the force of contractions should be monitored.
5. The oxytocin infusion should be discontinued immediately in the event of uterine hyperactivity or fetal distress. Oxygen should be administered to the mother. The mother and the fetus must be evaluated by the responsible physician.

B. Control of Postpartum Uterine Bleeding

1. Intravenous Infusion (Drip Method):
  To control postpartum bleeding, 10 to 40 units of oxytocin may be added to 1,000 mL of a nonhydrating diluent (physiologic electrolyte solution) and run a rate necessary to control uterine atony.
2. Intramuscular Administration:
  1 mL (10 units) of oxytocin can be given after the delivery of the placenta.

C. Treatment of Incomplete or Inevitable Abortion

Intravenous infusion with physiologic saline solution, 500 mL, or 5% dextrose in physiologic saline solution to which 10 units of oxytocin have been added should be infused at a rate of 20 to 40 drops per minutes.

HOW SUPPLIED

Oxytocin Injection, USP (synthetic), 10 USP units per mL is packaged in single or multiple dose vial and supplied as follows:

NDC | Vial Size | Fill Volume | Usage | Package size
0641-6114-25 | 2 mL | 1 mL | Single Dose Vial | 25
0641-6115-25 | 10 mL | 10 mL | Multiple Dose Vial | 25

Store at 25°C (77°F); excursions permitted to 15–30°C (59-86°F) [See USP Controlled Room Temperature].

Do not freeze. Do not use if solution is discolored or contains a precipitate.

To report SUSPECTED ADVERSE REACTIONS, contact West-Ward Pharmaceutcial Corp. at 1-877-845-0689, or the FDA at 1-800-FDA-1088 or www.fda.gov/medwatch.

For Product Inquiry call 1-877-845-0689.

Manufactured by:
by Gland Pharma Limited
Hyderabad-India

Distributed by:

WEST-WARD
PHARMACEUTCIALS
Eatontown, NJ 07724 USA

Revised June 2011

462-604-00

PRINCIPAL DISPLAY PANEL

NDC 0641-6114-01
Oxytocin Injection, USP (synthetic)
10 USP Units/mL
For IV Infusion or IM Use
1 mL Single Dose Vial

PRINCIPAL DISPLAY PANEL

NDC 0641-6115-01
Oxytocin Injection, USP (synthetic)
10 USP Units/mL
For IV Infusion or IM Use
10 mL Multiple Dose Vial